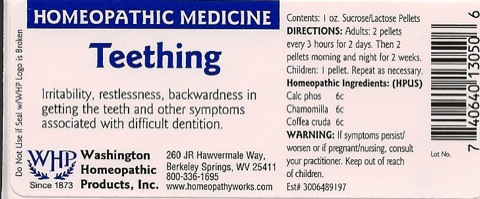 DRUG LABEL: Teething
NDC: 68428-005 | Form: PELLET
Manufacturer: Washington Homeopathic Products
Category: homeopathic | Type: HUMAN OTC DRUG LABEL
Date: 20191223

ACTIVE INGREDIENTS: TRIBASIC CALCIUM PHOSPHATE 6 [hp_C]/28 g; MATRICARIA RECUTITA 6 [hp_C]/28 g; ARABICA COFFEE BEAN 6 [hp_C]/28 g
INACTIVE INGREDIENTS: SUCROSE; LACTOSE

DRUG FACTS

ACTIVE INGREDIENTS

CALC PHOS 6C

CHAMOMILLA 6C

COFFEA CRUDA 6C

USES

To relieve the symptoms of irritability restlessness, backwardness in getting the teeth and other symptoms associated with difficult dentition..

KEEP OUT OF REACH OF CHILDREN

Keep this and all medicines out of reach of children.

INDICATIONS

CALC PHOS Stiffness

CHAMOMILLA Irritability

COFFEA CRUDA Sleeplessness

STOP USE AND ASK DOCTOR

If symptoms persist/worsen or if pregnant/nursing, stop use and consult your practitioner.

DIRECTIONS

Adults 2 pellets every 3 hours for 2 days. Then 2 pellets morning and night for 2 weeks.

Children: 1 pellet. Repeat as necessary.

INACTIVE INGREDIENTS

Sucrose/Lactose

PRINCIPAL DISPLAY PANEL

Enter section text here